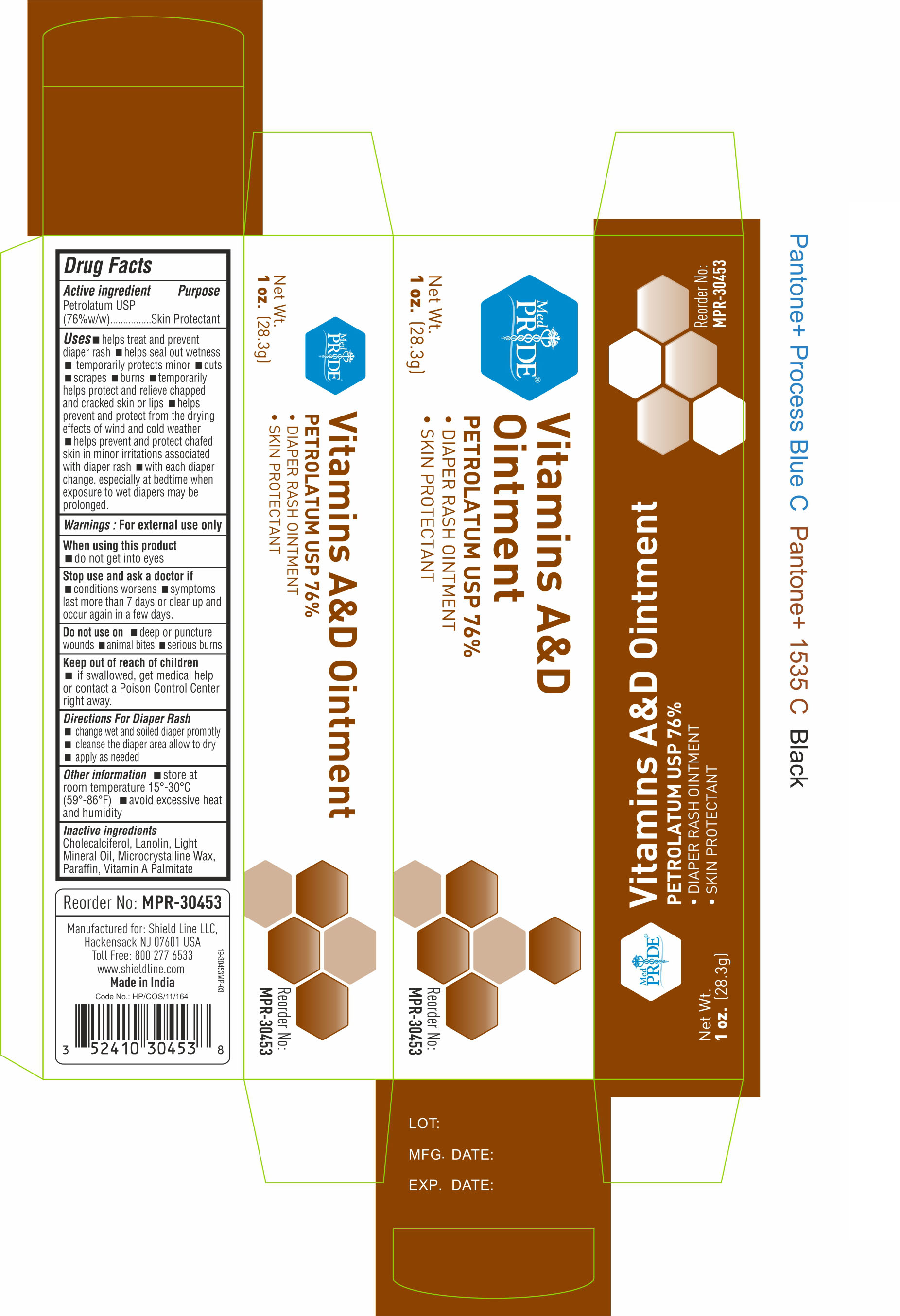 DRUG LABEL: MedPride
NDC: 52410-3045 | Form: OINTMENT
Manufacturer: Shield Line LLC
Category: otc | Type: HUMAN OTC DRUG LABEL
Date: 20250818

ACTIVE INGREDIENTS: PETROLATUM 76 g/100 g
INACTIVE INGREDIENTS: LANOLIN; MICROCRYSTALLINE WAX; LIGHT MINERAL OIL; VITAMIN A PALMITATE; CHOLECALCIFEROL; PARAFFIN

VITAMIN A&D MPR-30452

Active Ingredient

White Petroleum Jelly USP (76% w/w)

Purpose

Skin Protectant

Uses

■ helps treat and prevent diaper rash ■ helps seal out wetness ■ temporarily protects minor ■ cuts ■ scrapes ■ burns ■ temporarily helps protect and relieve chapped and cracked skin or lips ■ helps prevent and protect from the drying effects of wind and cold weather ■ helps prevent and protect chafed skin or minor skin irritations associated with diaper rash ■ with each diaper change, espicially at bedtime when exposure to wet diapers may be prolonged

Warnings

For external use only

When using this product

■ do not get into eyes

Stop use and ask a doctor if

■ condition worsens ■ symptoms last more than 7 days or clear up and occur again in a few days

Do not use on

■ animal bites ■ deep or puncture wounds ■ serious burns

Keep out of reach of children. If swallowed, get medical help or contact a Poison Control Center right away

Directions

for Diaper Rash ■ change wet and soiled diapers promptly ■ cleanse the diaper area and allow to dry ■ apply as needed

Other Information

■ store at 59-86F (15-30C) ■ avoid excessive heat and humidity

Inactive ingredients

Cholecalciferol, Lanolin, Light Mineral Oil, Microcrystalline Wax, Paraffin, Vitamin A Palmitate